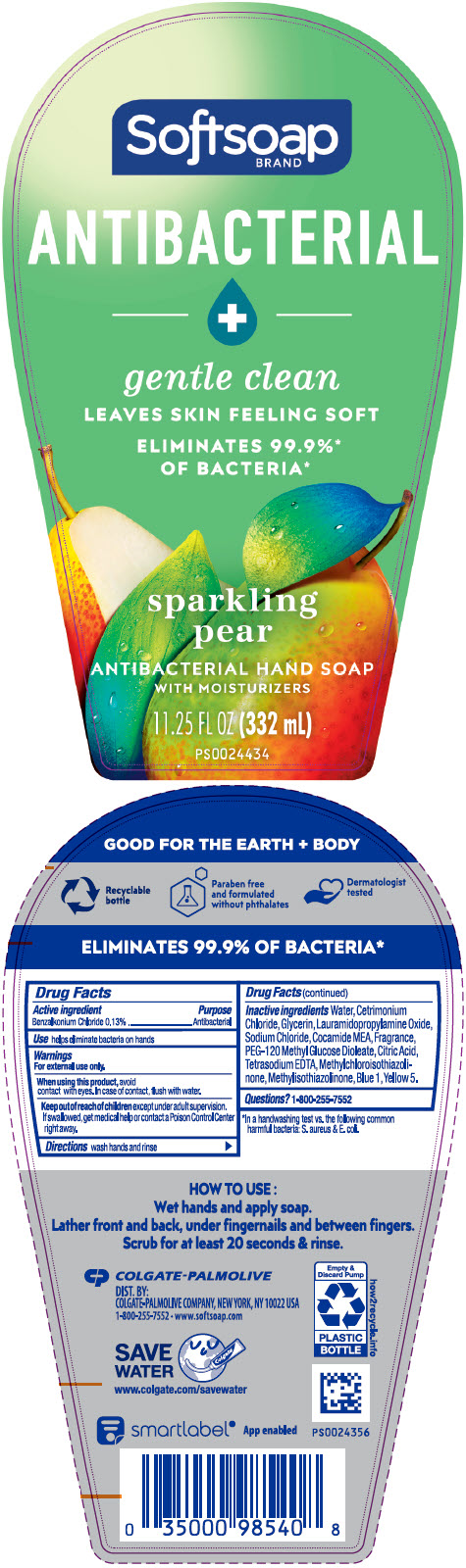 DRUG LABEL: Softsoap Antibacterial Sparkling Pear
NDC: 35000-102 | Form: LIQUID
Manufacturer: COLGATE PALMOLIVE COMPANY
Category: otc | Type: HUMAN OTC DRUG LABEL
Date: 20220414

ACTIVE INGREDIENTS: BENZALKONIUM CHLORIDE 1.33 mg/1 mL
INACTIVE INGREDIENTS: WATER; CETRIMONIUM CHLORIDE; GLYCERIN; LAURAMIDOPROPYLAMINE OXIDE; SODIUM CHLORIDE; COCO MONOETHANOLAMIDE; PEG-120 METHYL GLUCOSE DIOLEATE; CITRIC ACID MONOHYDRATE; EDETATE SODIUM; METHYLCHLOROISOTHIAZOLINONE; METHYLISOTHIAZOLINONE; FD&C BLUE NO. 1; FD&C YELLOW NO. 5

Softsoap Antibacterial Sparkling Pear

Drug Facts

Active ingredient

Benzalkonium Chloride 0.13%

Purpose

Antibacterial

Use

helps eliminate bacteria on hands

Warnings

For external use only.

When using this product, avoid contact with eyes. In case of contact, flush with water.

Keep out of reach of children except under adult supervision. If swallowed, get medical help or contact a Poison Control Center right away.

Directions

wash hands and rinse

Inactive ingredients

Water, Cetrimonium Chloride, Glycerin, Lauramidopropylamine Oxide, Sodium Chloride, Cocamide MEA, Fragrance, PEG-120 Methyl Glucose Dioleate, Citric Acid, Tetrasodium EDTA, Methylchloroisothiazolinone, Methylisothiazolinone, Blue 1, Yellow 5.

Questions?

1-800-255-7552

DIST. BY:
COLGATE-PALMOLIVE COMPANY, NEW YORK, NY 10022 USA

PRINCIPAL DISPLAY PANEL - 332 mL Bottle Label

Softsoap
BRAND

ANTIBACTERIAL
+

gentle clean

LEAVES SKIN FEELING SOFT

ELIMINATES 99.9%*
OF BACTERIA*

sparkling
pear

ANTIBACTERIAL HAND SOAP
WITH MOISTURIZERS

11.25 FL OZ (332 mL)

PS0024434